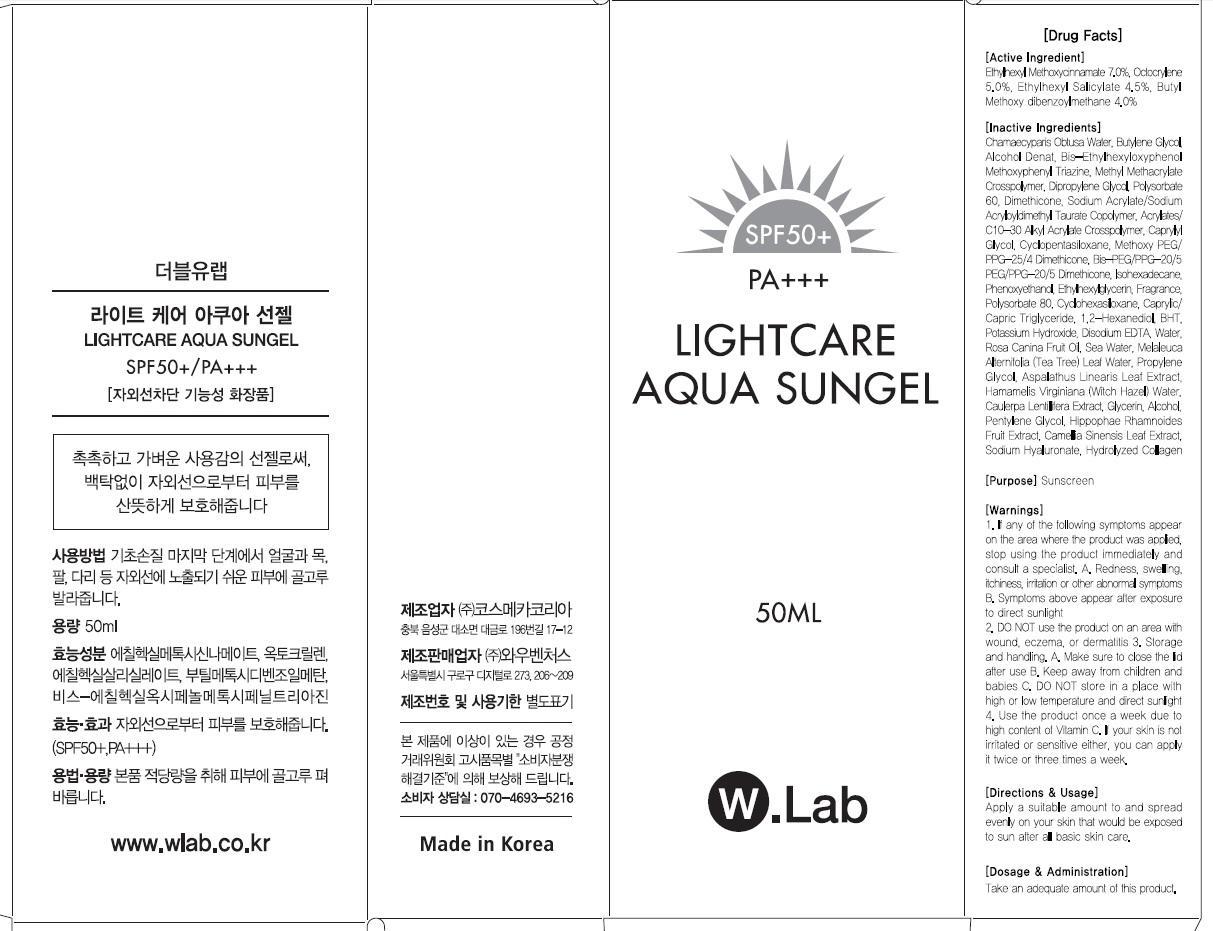 DRUG LABEL: LIGHT CARE AQUA SUN
NDC: 69894-100 | Form: GEL
Manufacturer: WOW VENTURES
Category: otc | Type: HUMAN OTC DRUG LABEL
Date: 20150624

ACTIVE INGREDIENTS: Octinoxate 3.5 mg/50 mL; Octocrylene 2.5 mg/50 mL; Octisalate 2.25 mg/50 mL; Avobenzone 2.0 mg/50 mL
INACTIVE INGREDIENTS: Butylene Glycol

ACTIVE INGREDIENT

Active Ingredient: Ethylhexyl Methoxycinnamate 7.0%, Octocrylene 5.0%, Ethylhexyl Salicylate 4.5%, Butyl Methoxydibenzoylmethane 4.0%

INACTIVE INGREDIENT

Inactive Ingredients: Chamaecyparis Obtusa Water, Butylene Glycol, Alcohol Denat., Bis-Ethylhexyloxyphenol Methoxyphenyl Triazine, Methyl Methacrylate Crosspolymer, Dipropylene Glycol, Polysorbate 60, Dimethicone, Sodium Acrylate/Sodium Acryloyldimethyl Taurate Copolymer, Acrylates/C10-30 Alkyl Acrylate Crosspolymer, Caprylyl Glycol, Cyclopentasiloxane, Methoxy PEG/PPG-25/4 Dimethicone, Bis-PEG/PPG-20/5 PEG/PPG-20/5 Dimethicone, Isohexadecane, Phenoxyethanol, Ethylhexylglycerin, Fragrance, Polysorbate 80, Cyclohexasiloxane, Caprylic/Capric Triglyceride, 1,2-Hexanediol, BHT, Potassium Hydroxide, Disodium EDTA, Water, Rosa Canina Fruit Oil, Sea Water, Melaleuca Alternifolia (Tea Tree) Leaf Water, Propylene Glycol, Aspalathus Linearis Leaf Extract, Hamamelis Virginiana (Witch Hazel) Water, Caulerpa Lentillifera Extract, Glycerin, Alcohol, Pentylene Glycol, Hippophae Rhamnoides Fruit Extract, Camellia Sinensis Leaf Extract, Sodium Hyaluronate, Hydrolyzed Collagen

PURPOSE

Purpose: Sunscreen

WARNINGS

Warnings: 1. If any of the following symptoms appear on the area where the product was applied, stop using the product immediately and consult a specialist. A. Redness, swelling, itchiness, irritation or other abnormal symptoms B. Symptoms above appear after exposure to direct sunlight 2. DO NOT use the product on an area with wound, eczema, or dermatitis 3. Storage and handling. A. Make sure to close the lid after use B. Keep away from children and babies C. DO NOT store in a place with high or low temperature and direct sunlight 4. Use the product once a week due to high content of Vitamin C. If your skin is not irritated or sensitive either, you can apply it twice or three times a week.

DESCRIPTION

Directions & Usage: Apply a suitable amount to and spread evenly on your skin that would be exposed to sun after all basic skin care.

Dosage & Administration: Take an adequate amount of this product.